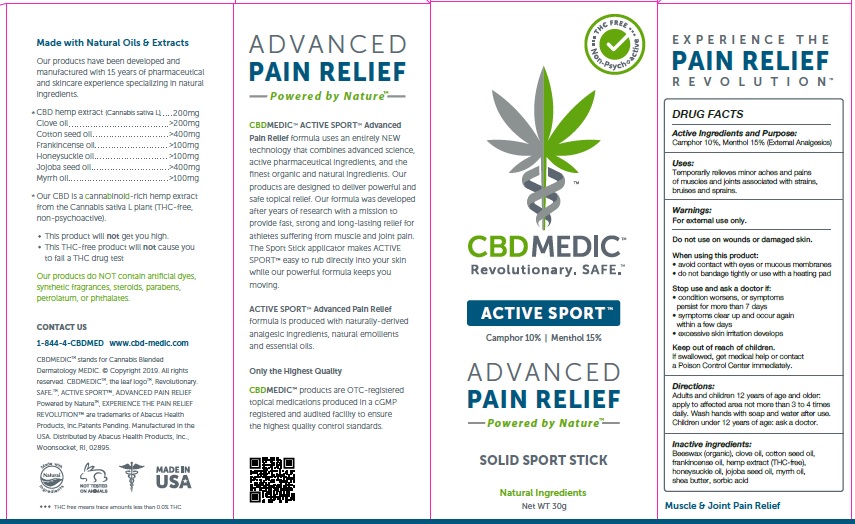 DRUG LABEL: CBDMEDIC Active Sport Pain Relief Stick
NDC: 24909-725 | Form: STICK
Manufacturer: AIDANCE SKINCARE & TOPICAL SOLUTIONS, LLC
Category: otc | Type: HUMAN OTC DRUG LABEL
Date: 20190304

ACTIVE INGREDIENTS: CAMPHOR (SYNTHETIC) 100 mg/1 g; MENTHOL 150 mg/1 g
INACTIVE INGREDIENTS: WHITE WAX; CLOVE OIL; COTTONSEED OIL; FRANKINCENSE OIL; HEMP; LONICERA CONFUSA WHOLE; JOJOBA OIL; MYRRH OIL; SHEA BUTTER; SORBIC ACID

CBDMEDIC Active Sport Pain Relief Stick

Active Ingredients and Purpose

Camphor 10%, Menthol 15% (External Analgesics)

Uses

Temporarily relieves minor aches and pains of muscles and joints associated with simple backache, arthritis, strains, bruises and sprains.

Warnings

For external use only. Do not use on wounds or damaged skin. When using this product: • avoid contact with eyes or mucous membranes • do not bandage tightly or use with a heating pad. Stop use and ask a doctor if: • condition worsens, or symptoms persist for more than 7 days • symptoms clear up and occur again within a few days • excessive skin irritation develops.

Keep out of reach of children

If swallowed, get medical help or contact a poison control center immediately.

Directions

Adults and children 12 years of age and older: apply to affected area not more than 3 to 4 times daily. Wash hands with soap and water after use. Children under 12 years of age: ask a doctor.

Inactive ingredients

Beeswax (organic), clove oil, cotton seed oil, frankincense oil, hemp extract (THC-free), honeysuckle oil, jojoba seed oil, myrrh oil, shea butter, sorbic acid